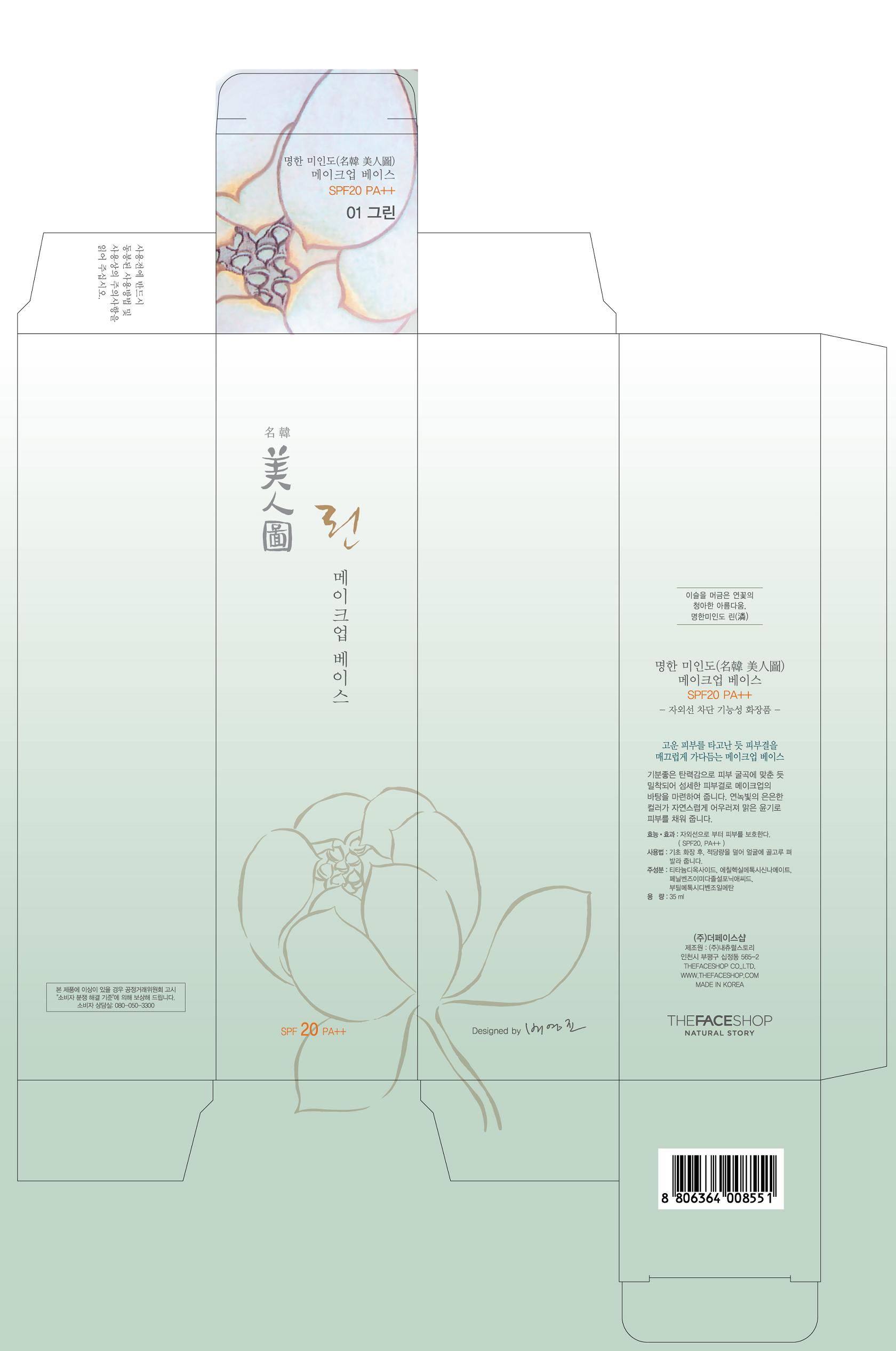 DRUG LABEL: Myung Han Miindo Make Up Base
NDC: 51523-100 | Form: LIQUID
Manufacturer: THEFACESHOP CO., LTD
Category: otc | Type: HUMAN OTC DRUG LABEL
Date: 20101015

ACTIVE INGREDIENTS: OCTINOXATE 6 mL/100 mL; TITANIUM DIOXIDE 3.4 mL/100 mL; ENSULIZOLE 2 mL/100 mL; AVOBENZONE 0.8 mL/100 mL
INACTIVE INGREDIENTS: CYCLOMETHICONE; PROPYLENE GLYCOL

Drug Facts

ACTIVE INGREDIENT

OCTINOXATE 6%, TITANIUM DIOXIDE 3.4%, ENSULIZOLE 2%, AVOBENZONE 0.8%

INACTIVE INGREDIENT

CYCLOMETHICONE, PROPYLENE GLYCOL.

PURPOSE

Provides high protection against sunburn and tanning.

WHEN USING

Keep out of eyes. Rinse with water to remove.

STOP USE

Rash or irritation develops and lasts.

DOSAGE AND ADMINISTRATION

Apply evenly before sun exposure and as needed.

PACKAGE LABEL

Myung Han Miindo

Make Up Base